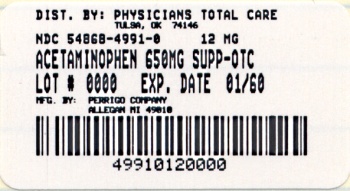 DRUG LABEL: ACETAMINOPHEN
NDC: 54868-4991 | Form: SUPPOSITORY
Manufacturer: Physicians Total Care, Inc.
Category: otc | Type: HUMAN OTC DRUG LABEL
Date: 20110413

ACTIVE INGREDIENTS: ACETAMINOPHEN 650 mg/1 1
INACTIVE INGREDIENTS: HYDROGENATED PALM KERNEL OIL

Active ingredient (in each rectal suppository)

Acetaminophen 650 mg

Purpose

Pain reliever/fever reducer

Uses

temporarily

- reduces fever
- relieves minor aches, pains, and headache

Warnings

Liver warning:

This product contains acetaminophen. Severe liver damage may occur if

- an adult or child 12 years and older takes more than 6 doses in 24 hours, which is the maximum daily amount
- taken with other drugs containing acetaminophen
- an adult takes 3 or more alcoholic drinks every day while using this product

For rectal use only

Do not use

- in children under 12 years
- if you are allergic to acetaminophen
- with any other drug containing acetaminophen (prescription or nonprescription). If you are not sure whether a drug contains acetaminophen, ask a doctor or pharmacist.

Ask a doctor before use if

- you have liver disease
- you are taking the blood thinning drug warfarin

Stop use and ask a doctor if

- fever lasts more than 3 days (72 hours), or recurs.
- pain gets worse or lasts more than 10 days.
- new symptoms occur.
- redness or swelling is present in the painful area.

These may be signs of a serious condition.

If pregnant or breast-feeding,

ask a health professional before use.

Keep out of reach of children.

If swallowed or in case of overdose, get medical help or contact a Poison Control Center right away. (1-800-222-1222) Quick medical attention is critical in case of overdose for adults and for children even if you do not notice any signs or symptoms.

Directions

- do not use more than directed
- remove wrapper
- carefully insert suppository well up into the rectum
- adults and children 12 years and older:
- 1 suppository every 4 to 6 hours while symptoms last
- do not exceed 6 suppositories in any 24 hour period
- children under 12 years: ask a doctor

Other information

- tamper-evident: suppositories are individually wrapped. Do not use if printed wrapper is opened or damaged.
- store at 20°-25°C (68°-77°F) or in a cool place

Inactive ingredients

hydrogenated vegetable oil

Questions or comments?

1-800-719-9260

PRINCIPAL DISPLAY PANEL

Acetaminophen Suppositories USP, 650 mg

NDC 54868-4991-0

Pain Reliever/Fever Reducer

See New Warnings Information

Read and Keep Carton for New Liver Warning

650 mg Each